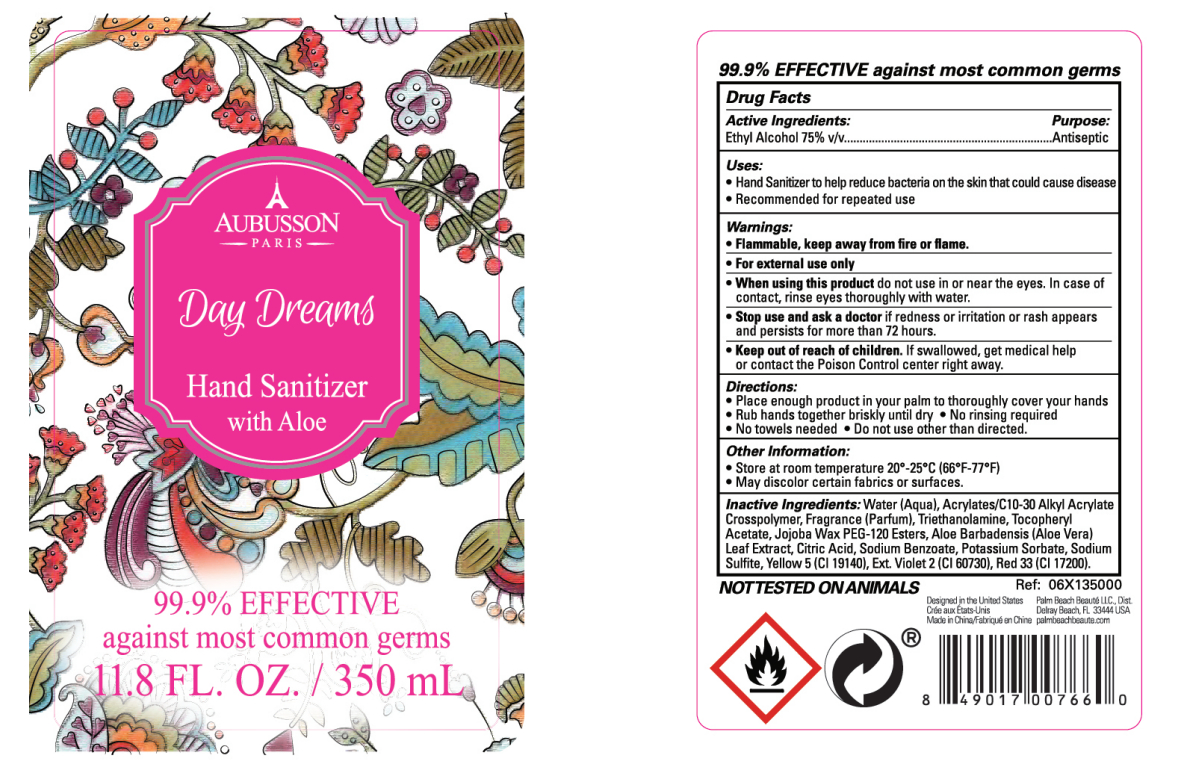 DRUG LABEL: Aubusson Day Dream Hand Sanitizer
NDC: 77218-001 | Form: GEL
Manufacturer: Palm Beach Beaute, LLC
Category: otc | Type: HUMAN OTC DRUG LABEL
Date: 20200424

ACTIVE INGREDIENTS: ALCOHOL 262.5 mL/350 mL
INACTIVE INGREDIENTS: .ALPHA.-TOCOPHEROL ACETATE; ALOE VERA LEAF; 3-HEXENYL SALICYLATE, CIS-; D&C RED NO. 33; TROLAMINE; SODIUM SULFITE; EXT. D&C VIOLET NO. 2; PROPIONALDEHYDE; SODIUM BENZOATE; WATER; CITRIC ACID MONOHYDRATE; POTASSIUM SORBATE; FD&C YELLOW NO. 5

DOSAGE AND ADMINISTRATION

Store at room temperature 20*. 25°C (66*F-77*F)

INACTIVE INGREDIENT

Aqua, Acrylates/C10-30 Alkyl Acrylate Crosspolymer, Triethanolamine, Tocopheryl Acetate, Jojoba Wax PEG-120 Esters, Aloe Barbadensis Leaf Extract, Citric Acid, Sodium Benzoate, Potassium Sorbate, Sodium Sulfite, CI 19140, CI 60730, CI 17200, 1,3,4,6,7,8-hexahydro-4,6,6,7,8,8-hexamethylindeno[5,6-c]pyran,α-methyl-1,3-benzodioxole-5-propionaldehyde, (Z)-3-hexenyl salicylate.

INDICATIONS AND USAGE

1.Place enough product in your palm to thoroughly cover your hands
2.Rub hands together briskly until dry●No rinsing required
3.No towels needed●Do not use other than directed.

ACTIVE INGREDIENT

Alcohol

keep out of children

PURPOSE

Disinfection
Sterilization
No Rinseing

WARNINGS

1.Flammable, keep away from fire or flame.
2.For external use only
3.When using this product do not use in or near the eyes. In case of contact, rinse eyes thoroughly with water.
4.Stop use and ask a doctor if redness or rritation or rash appears and persists for more than 72 hours.
5.Keep out of reach of children. If swallowed, get medical help or contact the Poison Control center right away.